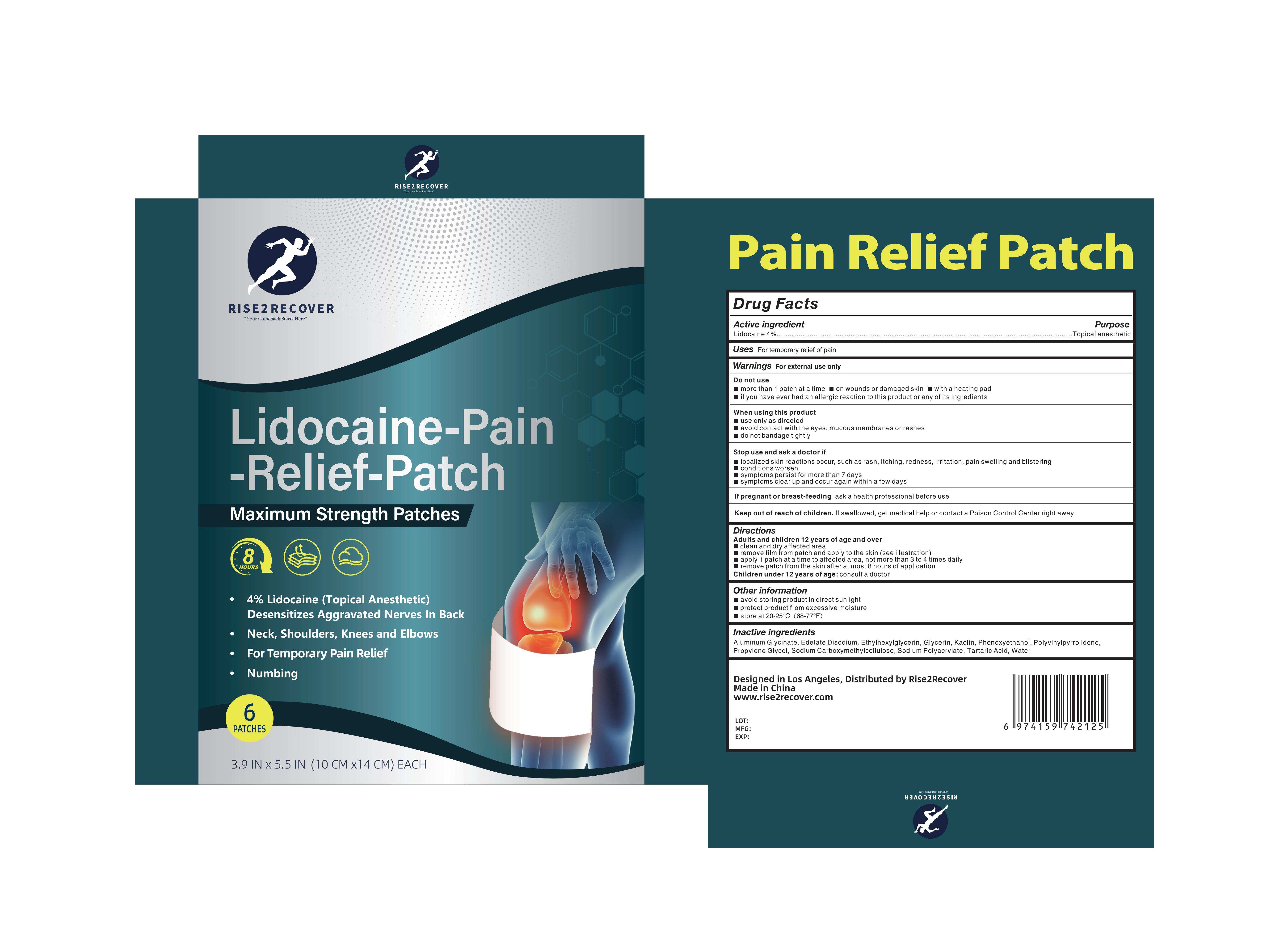 DRUG LABEL: Lidocaine-Pain-Relief-Patch
NDC: 83559-011 | Form: PATCH
Manufacturer: Henan Enokon Medical Instrument Co., Ltd.
Category: otc | Type: HUMAN OTC DRUG LABEL
Date: 20250914

ACTIVE INGREDIENTS: LIDOCAINE 4 g/100 1
INACTIVE INGREDIENTS: WATER; EDETATE DISODIUM; POVIDONE, UNSPECIFIED; SODIUM ACRYLATE; TARTARIC ACID; ALUMINUM GLYCINATE; ETHYLHEXYLGLYCERIN; PROPYLENE GLYCOL; GLYCERIN; PHENOXYETHANOL; KAOLIN; CARBOXYMETHYLCELLULOSE SODIUM

83559-011

Active Ingredient

Lidocaine 4%

Purpose

Topical anesthetic

Use

For temporary relief of pain

Warnings

For external use only

Do not use

more than 1 patch at a time
on wounds or damaged skin
with a heating pad
if you have ever had an allergic reaction to this product or any of its ingredients

When Using

When using this product
use only as directed
avoid contact with the eyes, mucous membranes or rashes
do not bandage tightly

Stop Use

Stop use and ask a doctor if
localized skin reaction occur,such as rash,itching,redness,irriation,pain swelling and blistering
conditions worsen
sympyoms persist for more than 7 days
sympyoms clear up and occur again within a few days

Ask Doctor

If pregnant or breast-feeding, ask a health professional before use.
Children under age of 12: Consult a doctor

Keep Out Of Reach Of Children

If swallowed , get medical help or contact with Poison Control Center right away.

Directions

Adults and children above 12 years old and over
clean and dry the affected area.
remove film from patch and apply to the skin (see illustration)
apply 1 patch at a time to affected area,not more than 3 to 4 times daily
remove patch from the skin after at most 8 hours of application.
Children under 12 years of age: consult a doctor

Other information

avoid storing product in direct sunlight
protect product from excessiver moisture
store at 20-25℃ (68-77℉)

Inactive ingredients

Aluminum Glycinate,Edetate Disodium,Ethylhexylglycerin,Glycerin,Kaolin,Phenoxyethanol,Polyvinylpyrrolidone,Propylene,Sodium Carboxymethylcellulose,Sodium Polyacrylate, Tartaric Acid, Water